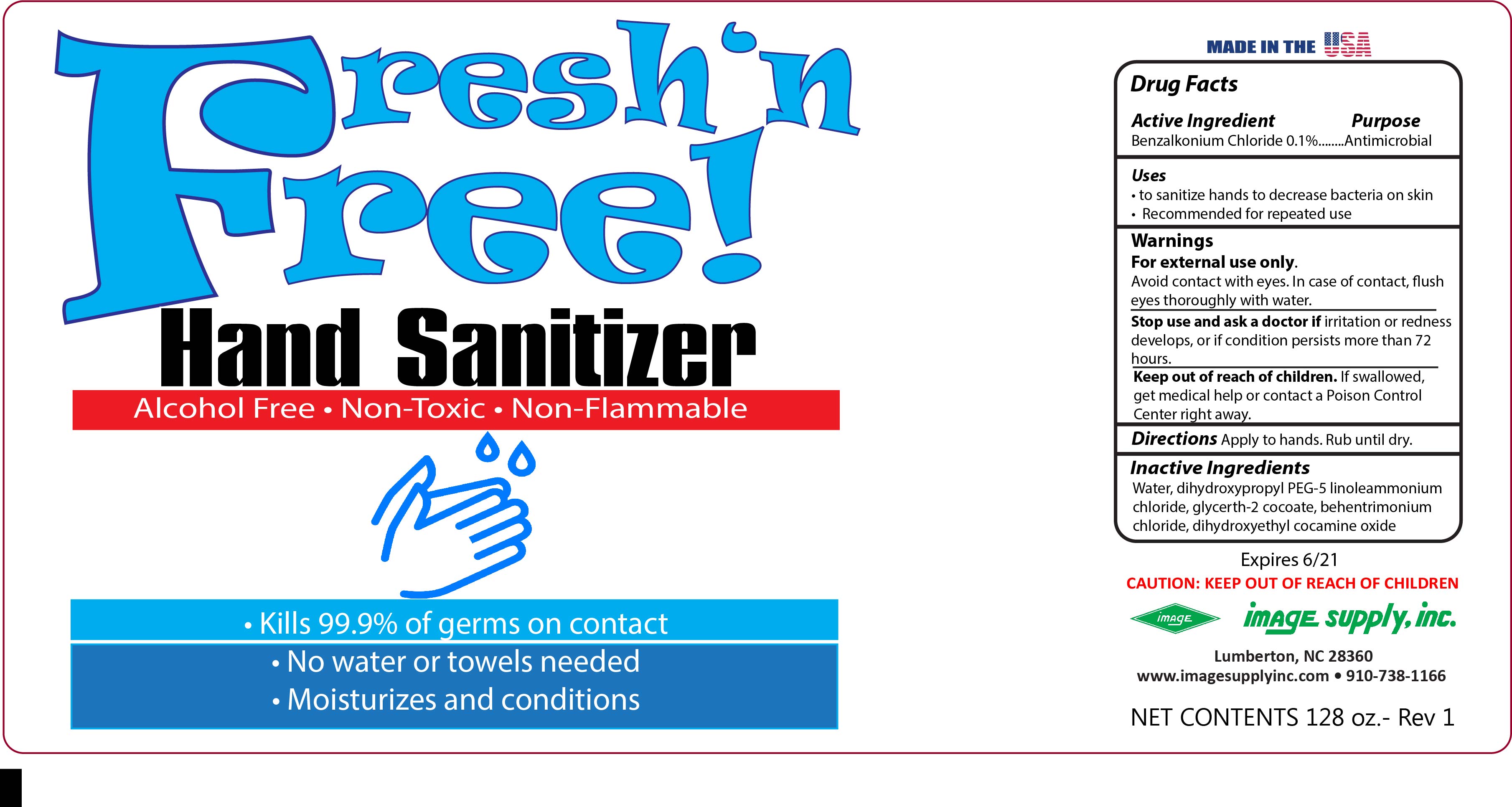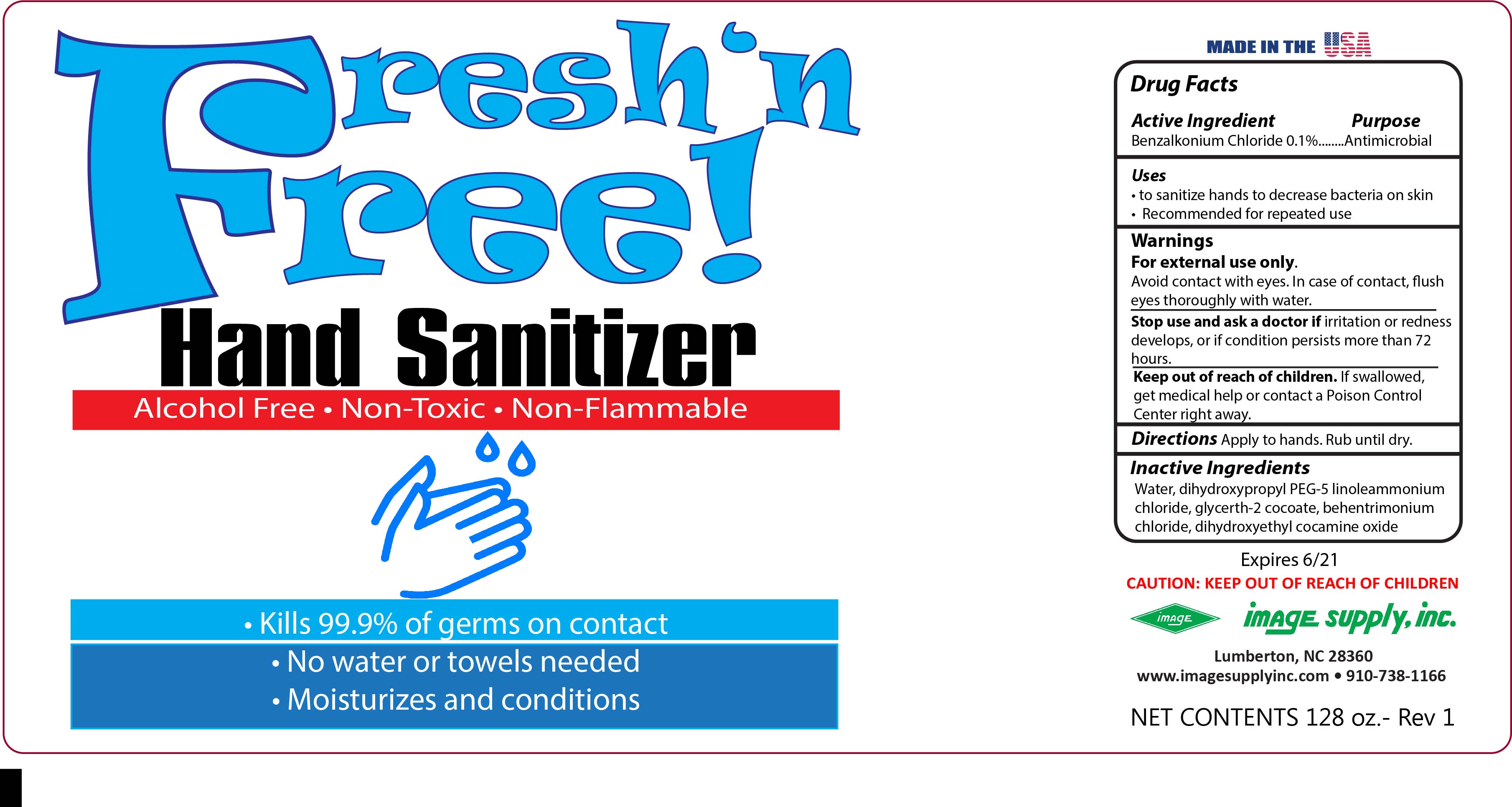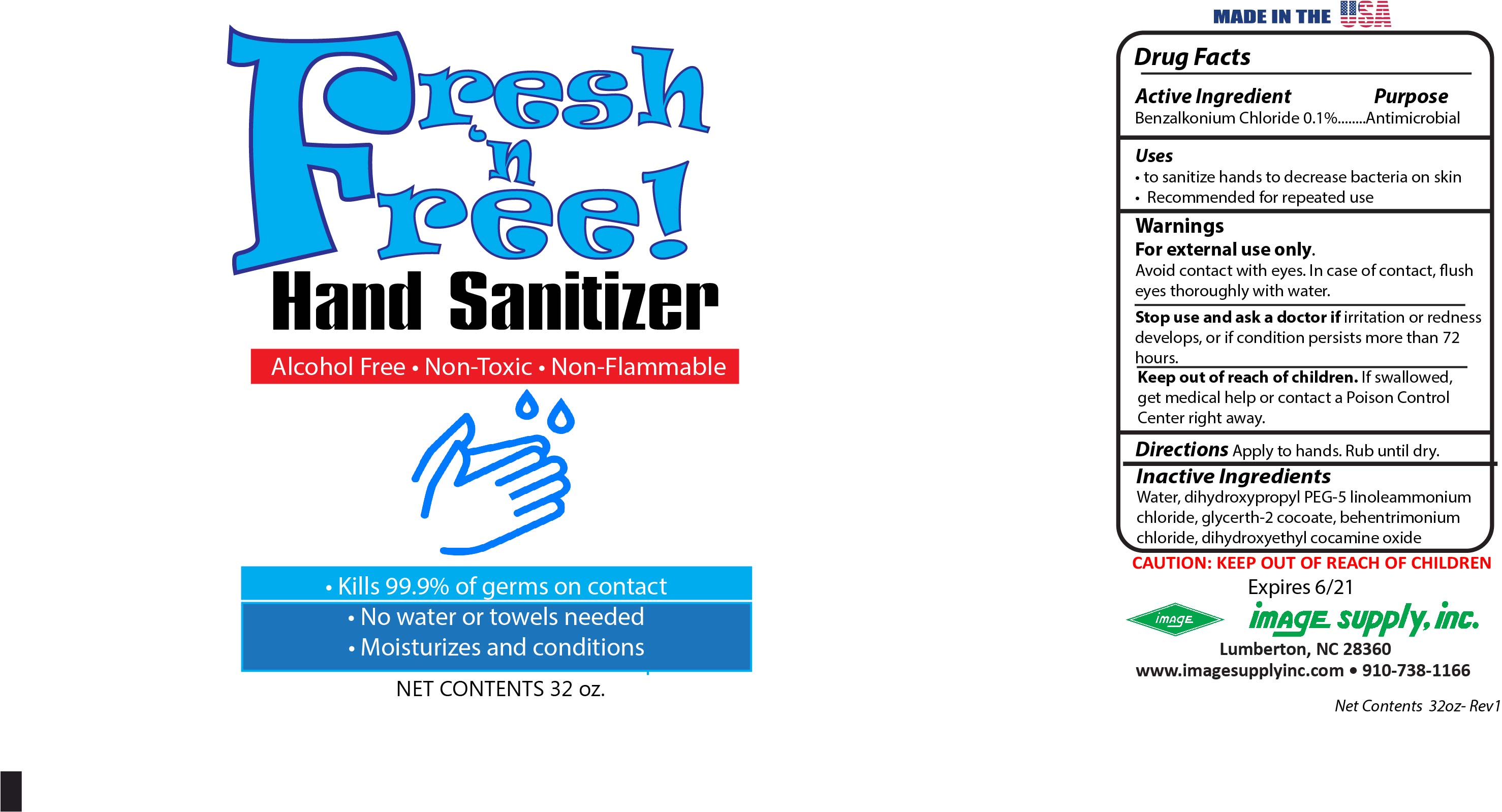 DRUG LABEL: Fresh N Free
NDC: 16496-001 | Form: SPRAY
Manufacturer: Image Supply, Inc
Category: otc | Type: HUMAN OTC DRUG LABEL
Date: 20200512

ACTIVE INGREDIENTS: BENZALKONIUM CHLORIDE 0.1 mg/1 mL
INACTIVE INGREDIENTS: GLYCERETH-2 COCOATE; BEHENTRIMONIUM CHLORIDE; DIHYDROXYETHYL COCAMINE OXIDE; WATER; DIHYDROXYPROPYL PEG-5 LINOLEAMMONIUM CHLORIDE

Uses

• to sanitize hands to decrease bacteria on skin
• Recommended for repeated use

Warnings

For external use only.
Avoid contact with eyes. In case of contact, flush
eyes thoroughly with water.

ASK DOCTOR

For external use only.
Avoid contact with eyes. In case of contact, flush
eyes thoroughly with water.

Keep out of reach of children. If swallowed,
get medical help or contact a Poison Control
Center right away.

Directions

Apply to hands. Rub until dry.

Inactive Ingredients

Water, dihydroxypropyl PEG-5 linoleammonium chloride, glycerth-2 cocoate, behentrimonium chloride, dihydroxyethyl cocamine oxide

Bottle Label Quart

946.353 ml NDC: 16496-001-03

PACKAGE LABEL

3785.41ml NDC:16496-001-0